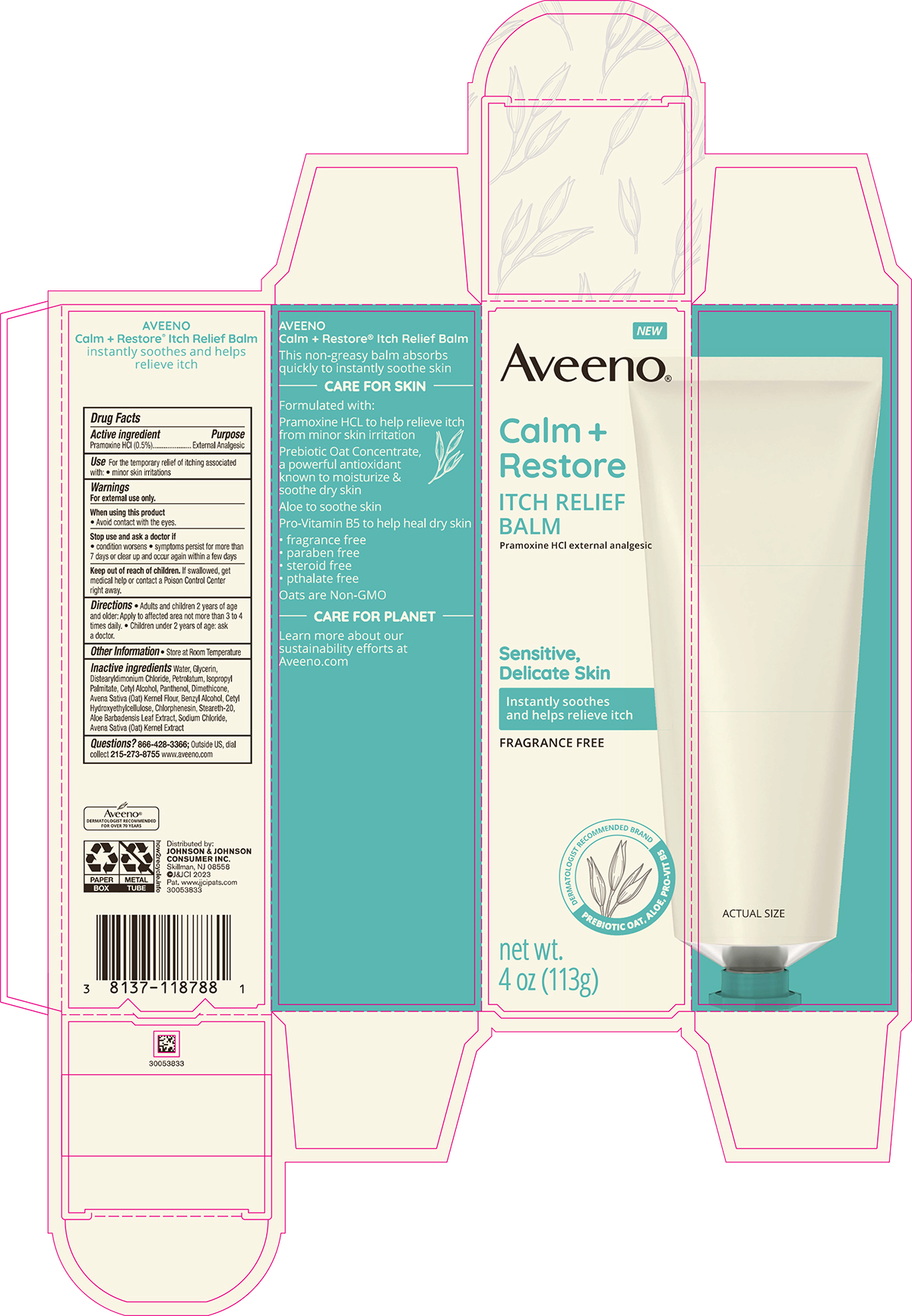 DRUG LABEL: Aveeno Calm Plus Restore Itch Relief Balm
NDC: 69968-0796 | Form: CREAM
Manufacturer: Kenvue Brands LLC
Category: otc | Type: HUMAN OTC DRUG LABEL
Date: 20241105

ACTIVE INGREDIENTS: PRAMOXINE HYDROCHLORIDE 5 mg/1 g
INACTIVE INGREDIENTS: WATER; GLYCERIN; DISTEARYLDIMONIUM CHLORIDE; PETROLATUM; CETYL ALCOHOL; BENZYL ALCOHOL; SODIUM CHLORIDE; PANTHENOL; ALOE VERA LEAF; STEARETH-20; CHLORPHENESIN; DIMETHICONE; OATMEAL; ISOPROPYL PALMITATE; OAT

Aveeno Calm Plus Restore Itch Relief Balm

Drug Facts

Active ingredient

Pramoxine HCl (0.5%)

Purpose

External Analgesic

Uses

For the temporary relief of itching associated with:

- minor skin irritations

Warnings

For external use only.

When using this product

- Avoid contact with the eyes.

Stop use and ask a doctor if

- condition worsens
- symptoms persist for more than 7 days or clear up and occur again within a few days

Keep out of reach of children. If swallowed, get medical help or contact a Poison Control Center right away.

Directions

- Adults and children 2 years of age and older: Apply to affected area not more than 3 to 4 times daily.
- Children under 2 years of age: ask a doctor.

Other Information

- Store at Room Temperature

Inactive ingredients

Water, Glycerin, Distearyldimonium Chloride, Petrolatum, Isopropyl Palmitate, Cetyl Alcohol, Panthenol, Dimethicone, Avena Sativa (Oat) Kernel Flour, Benzyl Alcohol, Cetyl Hydroxyethylcellulose, Chlorphenesin, Steareth-20, Aloe Barbadensis Leaf Extract, Sodium Chloride, Avena Sativa (Oat) Kernel Extract

Questions?

866-428-3366; Outside US, dial collect 215-273-8755 www.aveeno.com

Distributed by:
JOHNSON & JOHNSON
CONSUMER INC.
Skillman, NJ 08558

PRINCIPAL DISPLAY PANEL - 113g Tube Carton

NEW

Aveeno®

Calm +

Restore

ITCH RELIEF

BALM

Pramoxine HCl external analgesic

Sensitive,

Delicate Skin

Instantly soothes

and helps relieve itch

FRAGRANCE FREE

DERMATOLOGIST RECOMMENDED BRAND

PREBIOTIC OAT, ALOE, PRO-VIT B5

net wt.

4 OZ (113 g)